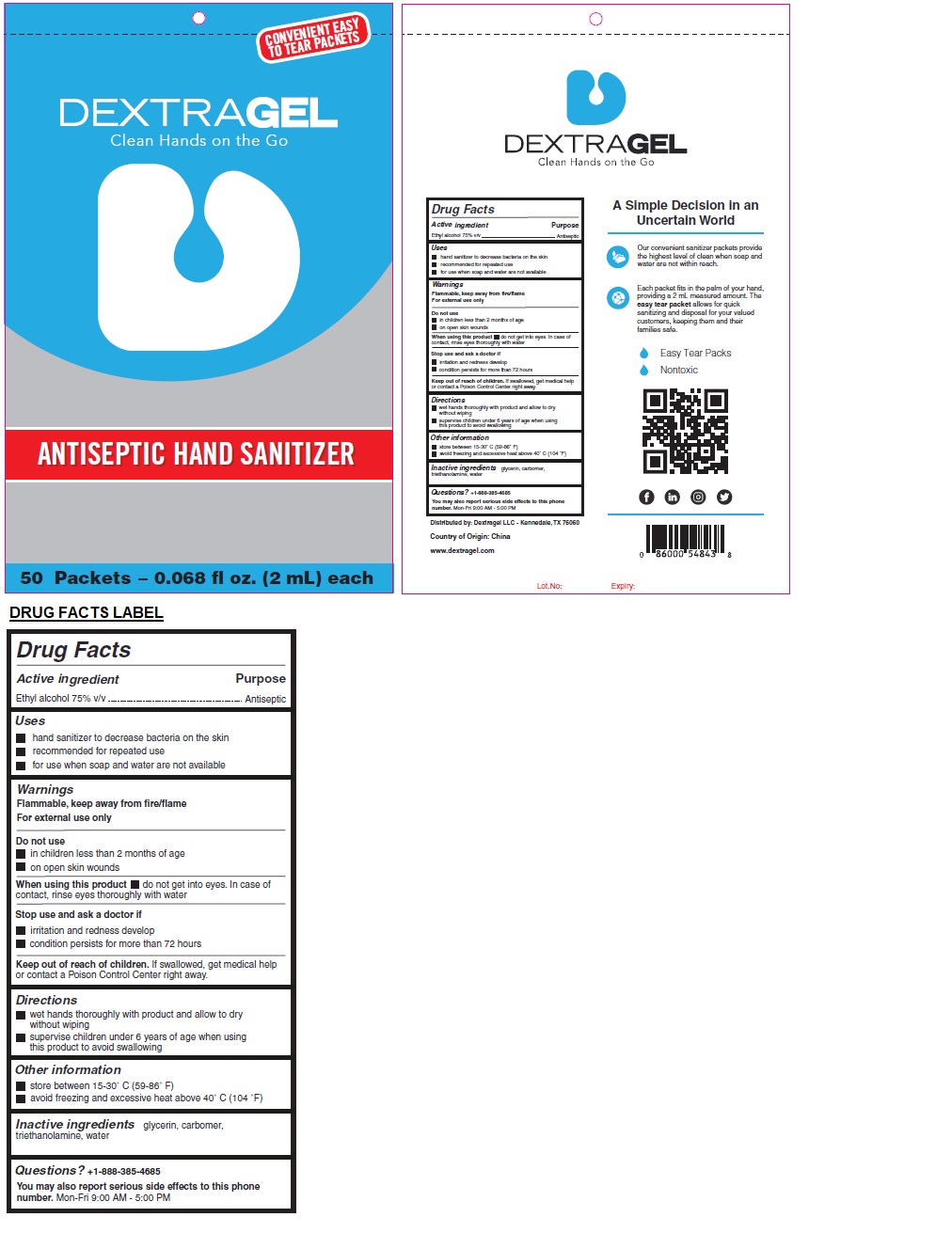 DRUG LABEL: DEXTRAGEL ANTISEPTIC HAND SANITIZER
NDC: 80209-098 | Form: GEL
Manufacturer: Dextra Gel, Llc
Category: otc | Type: HUMAN OTC DRUG LABEL
Date: 20201201

ACTIVE INGREDIENTS: ALCOHOL 75 mL/100 mL
INACTIVE INGREDIENTS: GLYCERIN; CARBOMER HOMOPOLYMER, UNSPECIFIED TYPE; TROLAMINE; WATER

DEXTRAGEL ANTISEPTIC HAND SANITIZER

Active ingredient

Ethyl alcohol 75% v/v

Purpose

Antiseptic

Uses

- hand sanitizer to decrease bacteria on the skin
- recommended for repeated use
- for use when soap and water are not available

Warnings

Flammable, keep away from fire/flame

For external use only

Do not use

- in children less than 2 months of age
- on open skin wounds

When using this product • do not get into eyes. In case of contact, rinse eyes thoroughly with water

Stop use and ask a doctor if

- irritation and redness develop
- condition persists for more than 72 hours

Keep out of reach of children. If swallowed, get medical help or contact a Poison Control Center right away.

Directions

- wet hands thoroughly with product and allow to dry without wiping
- supervise children under 6 years of age when using this product to avoid swallowing

Other information

- store between 15-30°C (59-86˚F)
- avoid freezing and excessive heat above 40˚C (104˚F)

Inactive ingredients

glycerin, carbomer, triethanolamine, water

Questions? +1-888-385-4685

You may also report serious side effects to this phone number. Mon-Fri 9:00 AM - 5:00 PM

CONVENIENT EASY TO TEAR PACKETS

Clean Hands on the Go

A Simple Decision in an Uncertain World

Our convenient sanitizer packets provide the highest level of clean when soap and water are not within reach.

Each packet fits in the palm of your hand, providing a 2 mL measured amount. The easy tear packet allows for quick sanitizing and disposal for your valued customers, keeping them and their families safe.

Easy Tear Packs

Nontoxic

Distributed by: Dextragel LLC - Kennedale, TX 76060

Country of origin: China

www.dextragel.com